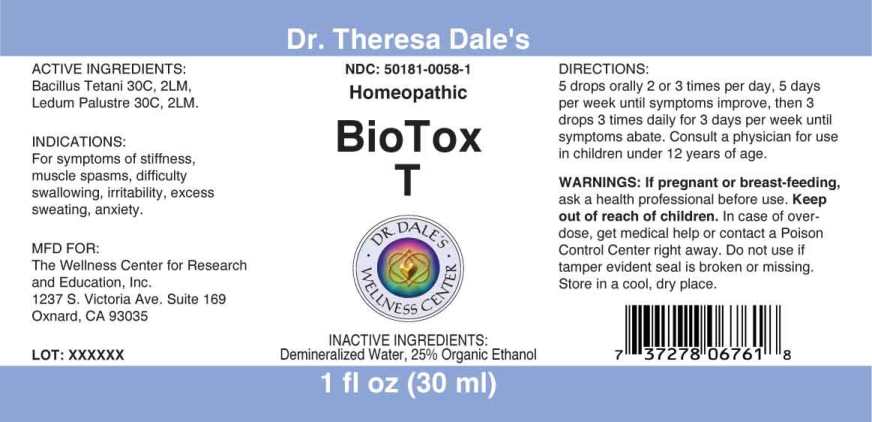 DRUG LABEL: BioTox T
NDC: 50181-0058 | Form: LIQUID
Manufacturer: The Wellness Center For Research and Education
Category: homeopathic | Type: HUMAN OTC DRUG LABEL
Date: 20250530

ACTIVE INGREDIENTS: CLOSTRIDIUM TETANI 30 [hp_C]/1 mL; RHODODENDRON TOMENTOSUM LEAFY TWIG 30 [hp_C]/1 mL
INACTIVE INGREDIENTS: WATER; ALCOHOL

Drug Facts:

ACTIVE INGREDIENTS:

Bacillus Tetani 30C, 2LM, Ledum Palustre 30C, 2LM.

INDICATIONS:

For symptoms of stiffness, muscle spasms, difficulty swallowing, irritability, excess sweating, anxiety.

WARNINGS:

If you are pregnant or breastfeeding, ask a health professional before use.

Keep out of reach of children. In case of overdose, get medical help or contact a Poison Control Center right away.

Do not use if tamper evident seal is broken or missing.

Store in a cool, dry place.

Keep out of reach of children. In case of overdose, get medical help or contact a Poison Control Center right away.

DIRECTIONS:

5 drops orally 2 or 3 times per day, 5 days per week until symptoms improve, then 3 drops 3 times daily for 3 days per week until symptoms abate. Consult a physician for use in children under 12 years of age.

INDICATIONS:

For symptoms of stiffness, muscle spasms, difficulty swallowing, irritability, excess sweating, anxiety.

INACTIVE INGREDIENTS:

Demineralized Water, 25% Organic Ethanol

QUESTIONS:

MFD FOR:

The Wellness Center for Research

and Education, Inc.

1237 S. Victoria Ave. Suite 169

Oxnard, CA 93035

PACKAGE LABEL DISPLAY:

Dr. Theresa Dale's

NDC 50181-0058-1

Homeopathic

BioTox

T

1 fl oz (30 ml)